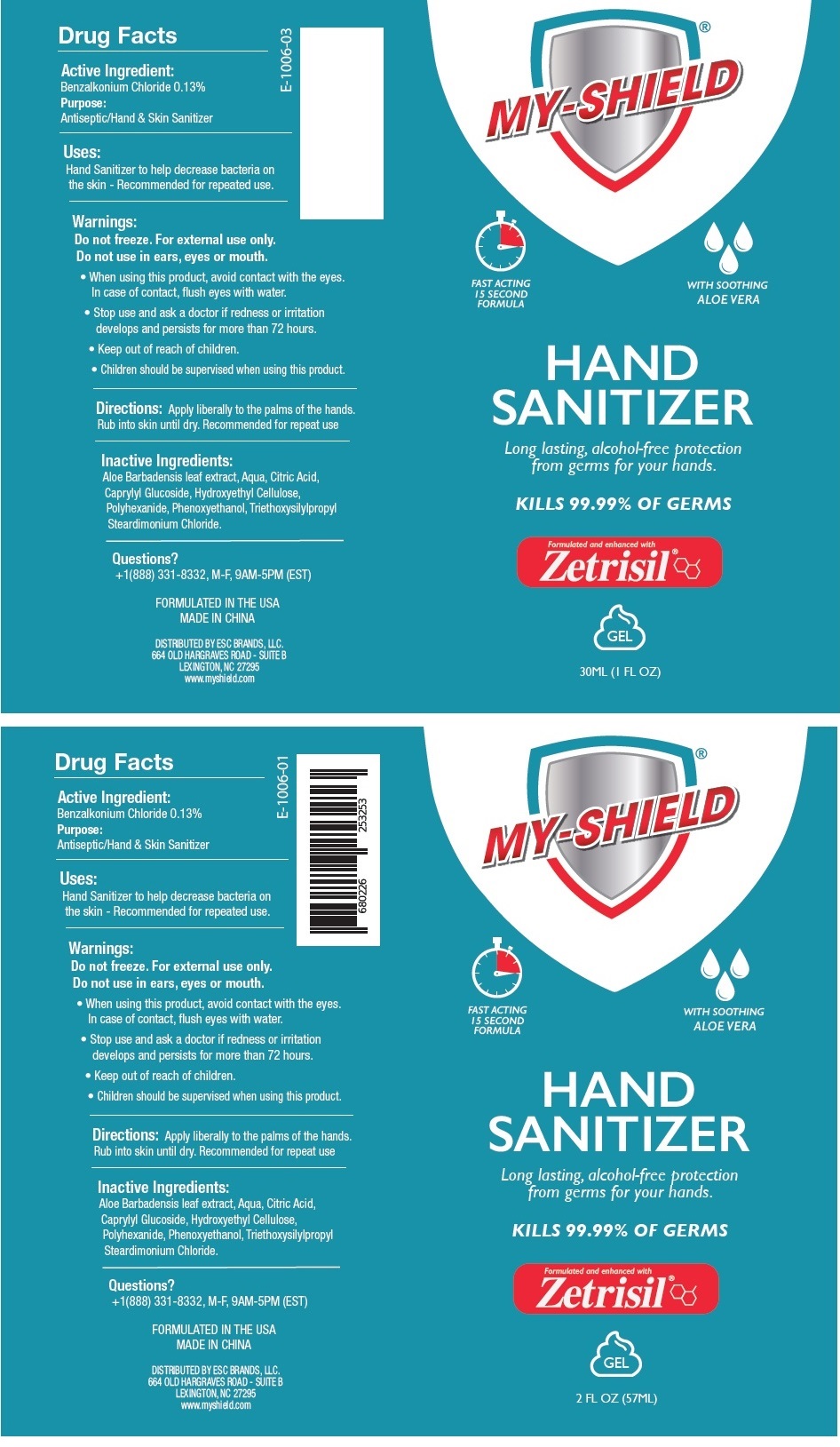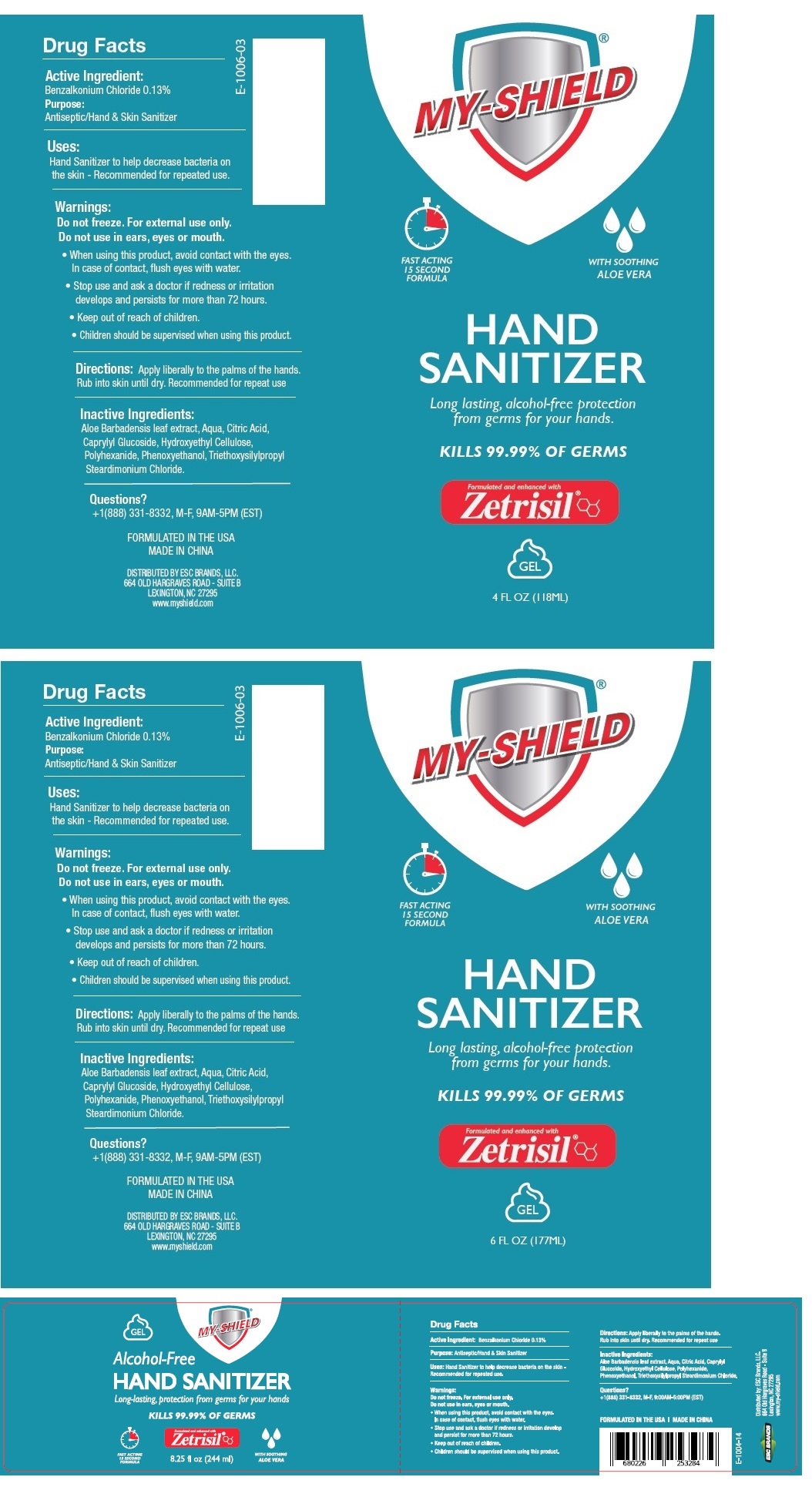 DRUG LABEL: My-Shield Hand Sanitizer Gel
NDC: 71884-011 | Form: GEL
Manufacturer: Enviro Specialty Chemicals Inc
Category: otc | Type: HUMAN OTC DRUG LABEL
Date: 20241231

ACTIVE INGREDIENTS: BENZALKONIUM CHLORIDE 0.13 g/100 mL
INACTIVE INGREDIENTS: ALOE VERA LEAF; WATER; CITRIC ACID MONOHYDRATE; CAPRYLYL GLUCOSIDE; HYDROXYETHYL CELLULOSE, UNSPECIFIED; POLIHEXANIDE; PHENOXYETHANOL; TRIETHOXYSILYLPROPYL STEARDIMONIUM CHLORIDE

MY-SHIELD HAND SANITIZER GEL

Active Ingredient:

Benzalkonium Chloride 0.13%

Purpose:

Antiseptic/Hand & Skin Sanitizer

Uses:

Hand Sanitizer to help decrease bacteria on the skin - Recommended for repeated use.

Warnings:

Do not freeze. For external use only.

Do not use in ears, eyes or mouth.

• When using this product, avoid contact with the eyes. In case of contact, flush eyes with water.

• Stop use and ask a doctor if redness or irritation develops and persists for more than 72 hours.

• Children should be supervised when using this product.

• Keep out of reach of children.

Directions:

Apply liberally to the palms of the hands. Rub into skin until dry. Recommended for repeat use

Inactive Ingredients:

Aloe Barbadensis leaf extract, Aqua, Citric Acid, Caprylyl Glucoside, Hydroxyethyl Cellulose,

Polyhexanide, Phenoxyethanol, Triethoxysilylpropyl Steardimonium Chloride.

Questions?

+1(888) 331-8332, M-F, 9AM-5PM (EST)

FAST ACTING 15 SECOND FORMULA

WITH SOOTHING ALOE VERA

Long lasting, alcohol-free protection from germs for your hands.

KILLS 99.99% OF GERMS

Formulated and enhanced with Zetrisil

FORMULATED IN THE USA

MADE IN CHINA

DISTRIBUTED BY ESC BRANDS, LLC.

664 OLD HARGRAVES ROAD - SUITE B

LEXINGTON, NC 27295

www.myshield.com